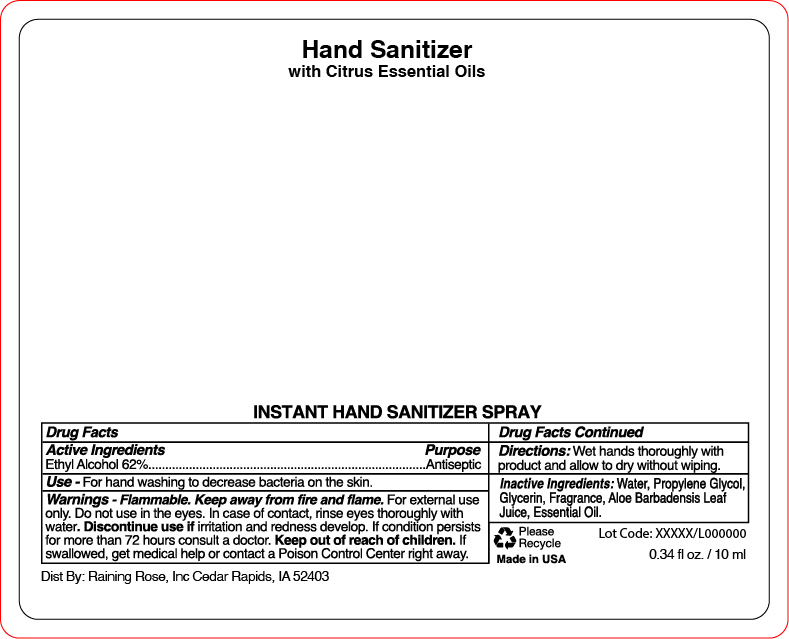 DRUG LABEL: Hand Sanitizer
NDC: 65692-2069 | Form: LIQUID
Manufacturer: Raining Rose
Category: otc | Type: HUMAN OTC DRUG LABEL
Date: 20210506

ACTIVE INGREDIENTS: ALCOHOL 62 mL/100 mL
INACTIVE INGREDIENTS: WATER; GLYCERIN; ALOE VERA LEAF; PROPYLENE GLYCOL

ACTIVE INGREDIENT

Ethyl Alcohol 62%

PURPOSE

Antiseptic

INDICATIONS AND USAGE

For hand washing to decrease bacteria on the skin.

WARNINGS

Flammable. Keep away from fire and flame. For external use only. Do not use in the eyes. In case of contact, rinse eyes thoroughly with water. Discontinue use if irritation and redness develop. If condition persists for more than 72 hours consult a doctor. If swallowed, get medical help or contact a Poison Control Center right away.

Keep out of reach of children

DOSAGE AND ADMINISTRATION

Wet hands thoroughly with product and allow to dry without wiping.

INACTIVE INGREDIENT

Water, Propylene Glycol, Glycerin, Fragrance, Aloe Barbadensis Leaf Juice, Essential Oil.